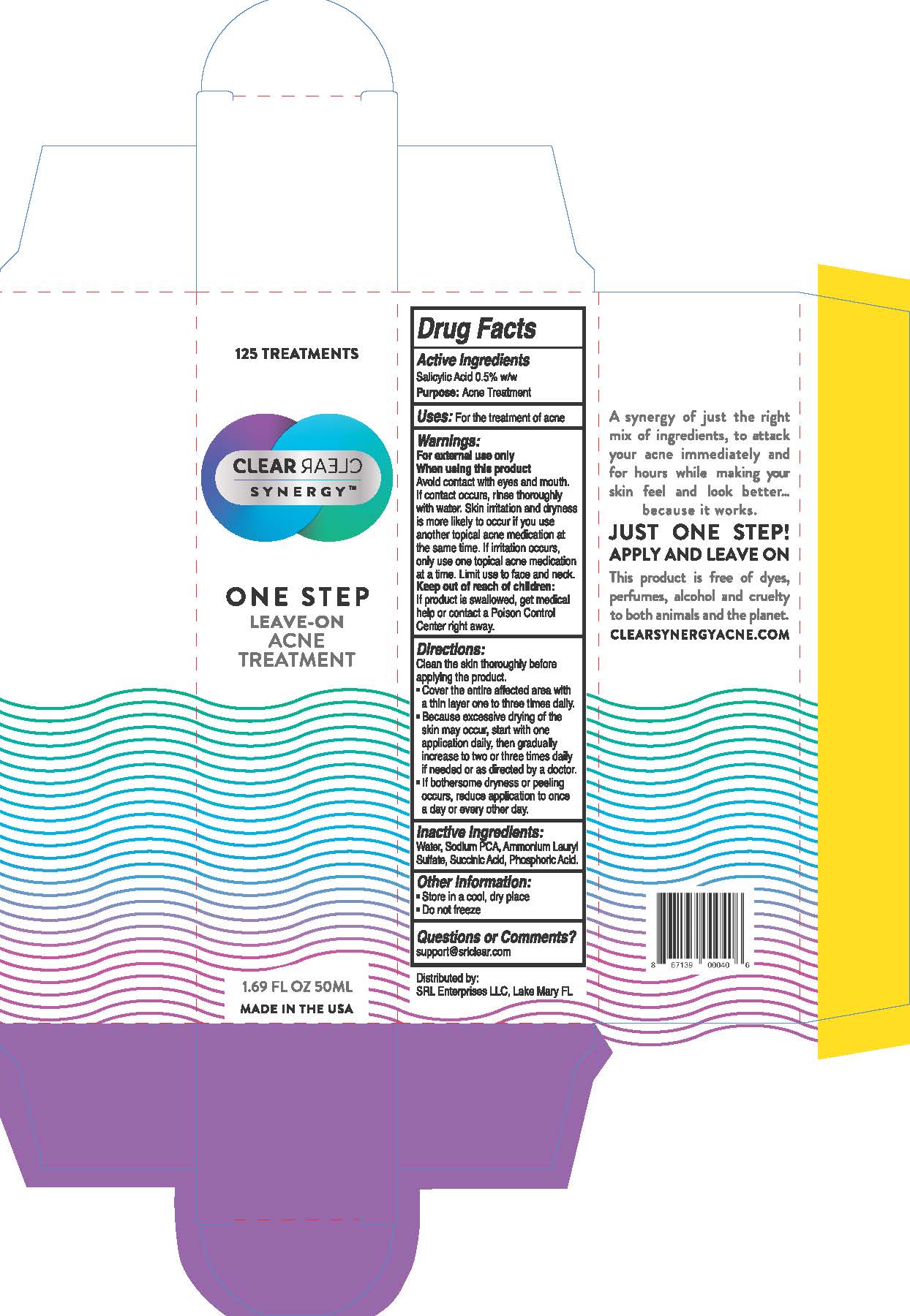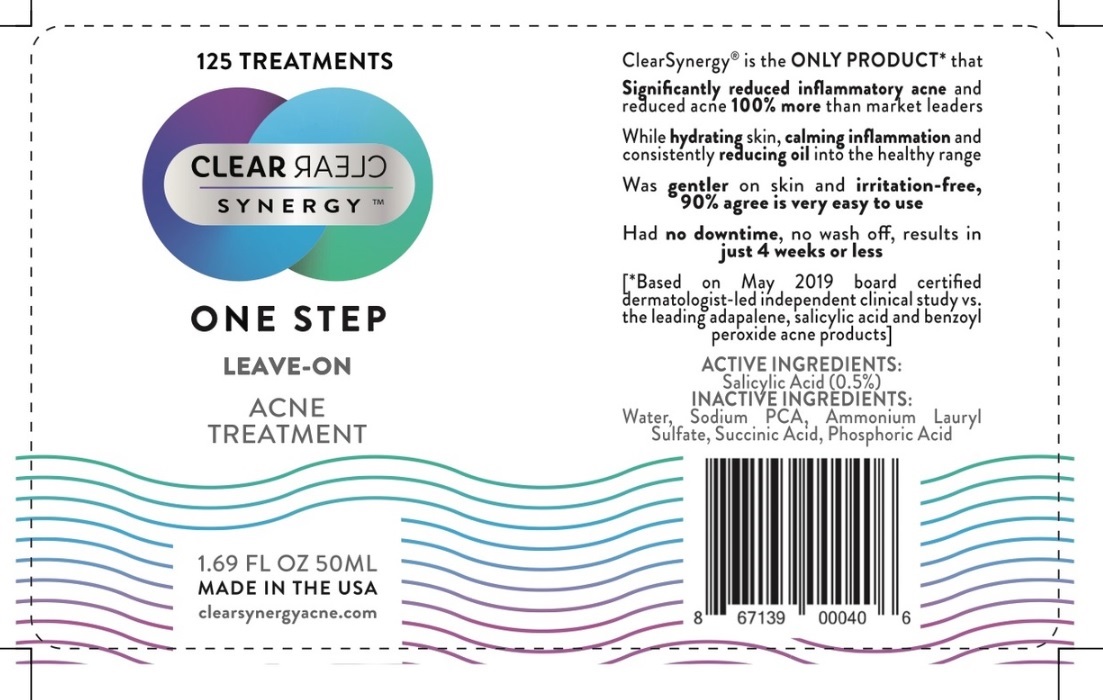 DRUG LABEL: CLEARSYNERGY
NDC: 71617-100 | Form: LIQUID
Manufacturer: SRL ENTERPRISES LLC
Category: otc | Type: HUMAN OTC DRUG LABEL
Date: 20251111

ACTIVE INGREDIENTS: SALICYLIC ACID 0.25 g/50 mL
INACTIVE INGREDIENTS: WATER; SODIUM PYRROLIDONE CARBOXYLATE; AMMONIUM LAURYL SULFATE; SUCCINIC ACID; PHOSPHORIC ACID

Drug Facts

Active Ingredients

Salicylic Acid 0.5% w/w

Purpose:Acne Treatment

INDICATIONS AND USAGE

Uses: For the treatment of acne

Warnings:

For external use only

When using this product

Avoid contact with eyes and mouth.

If contact occurs, rinse thoroughly

with water. Skin irritation and dryness

is more likely to occur if you use

another topical acen medication at

the same time. If irritation occurs,

only use one topical acne medication

at a time. Limit use to face and neck.

Keep out of reach of children:

If product is swallowed, get medical

help or contact a Poison Control

Center right away.

Directions:

Clean the skin thoroughly before

applying e product.

•Cover the entire affected area with

a thin layer one to three times daily.

•Because excessive drying of the

skin may occur, start with one

application daily, then gradually

increase to two to three times daily

if needed or as directed by a doctor.

•If bothersome dryness or peeling

occurs, reduce application to once

a day or every other day.

Inactive Ingredients:

Water, Sodium PCA, Ammonium Lauryl

Sulfate, Succinic Acid, Phospheric Acid.

Other information:

•Store in a cool, dry place

•Do not freeze

Questions or Comments?

support@srlclear.com